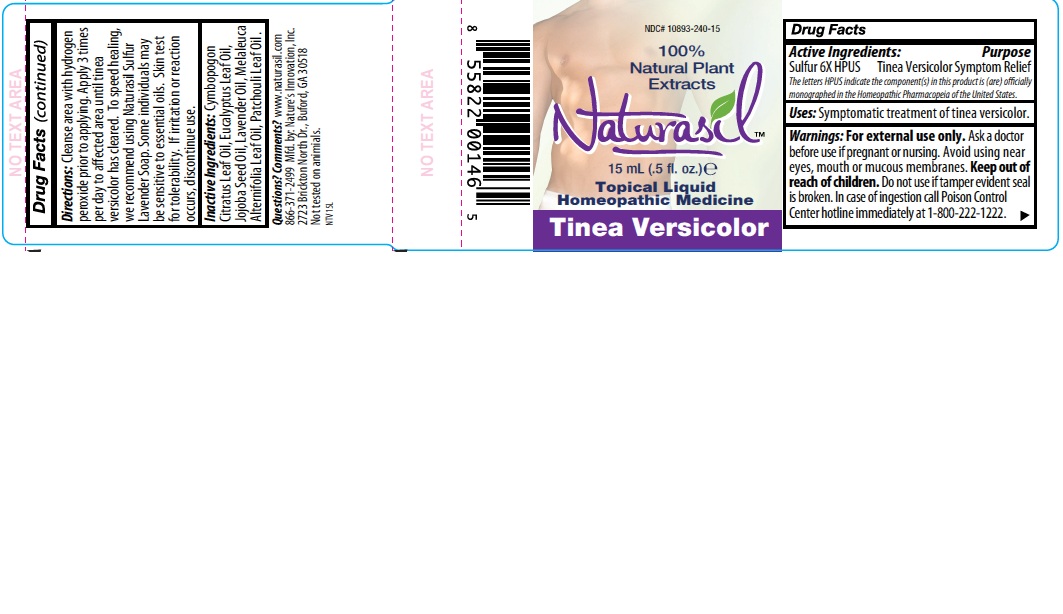 DRUG LABEL: Naturasil
NDC: 10893-240 | Form: LIQUID
Manufacturer: Nature's Innovation, Inc.
Category: homeopathic | Type: HUMAN OTC DRUG LABEL
Date: 20210114

ACTIVE INGREDIENTS: SULFUR 6 [hp_X]/1 mL
INACTIVE INGREDIENTS: WEST INDIAN LEMONGRASS OIL; EUCALYPTUS OIL; JOJOBA OIL; LAVENDER OIL; TEA TREE OIL; PATCHOULI OIL

Tinea Versicolor Label

Drug Facts

Active Ingredients:

Sulfur 6X HPUS

DESCRIPTION

The letters HPUS indicate the component(s) in this product is (are) officially monographed in the Homeopathic Pharmacopeia of the United States.

Purpose

Tinea Versicolor

Symptom Relief

INDICATIONS AND USAGE

Uses: Symptomatic treatment of tinea versicolor.

Warnings: For external use only.

Ask a doctor before use if pregnant or nursing.

OTHER SAFETY INFORMATION

Avoid using near eyes, mouth or mucous membranes.

Keep out of reach of children.

Do not use if tamper evident seal is broken.

OTHER SAFETY INFORMATION

In case of ingestion call Poison Control Center hotline immediately at 1-800-222-1222.

DOSAGE AND ADMINISTRATION

Directions: Cleanse area with hydrogen peroxide prior to applying. Apply 3 times per day to affected area until tinea versicolor has cleared. To speed healing, we recommend using Naturasil Sulfur Lavender Soap. Some individuals may be sensitive to essential oils. Skin test for tolerability. If irritation or reaction occurs, discontinue use.

INACTIVE INGREDIENT

Inactive Ingredients: Cymbopogon Citratus Leaf Oil, Eucalyptus Leaf Oil, Jojoba Seed Oil, Lavender Oil, Melaleuca Alternifolia Leaf Oil, Patchouli Leaf Oil.

Questions? Comments?

www.naturasil.com 1-866-371-2499

Mfd. by: Nature's Innovation, Inc.,

2723 Brickton North Dr., Buford, GA 30518

Not tested on animals.

PACKAGE LABEL

NDC# 10893-240-15

100%

Natural Plant

Extracts

Naturasil

15 ml (.5 fl. oz.)

Topical Liquid

Homeopathic Medicine

Tinea Versicolor